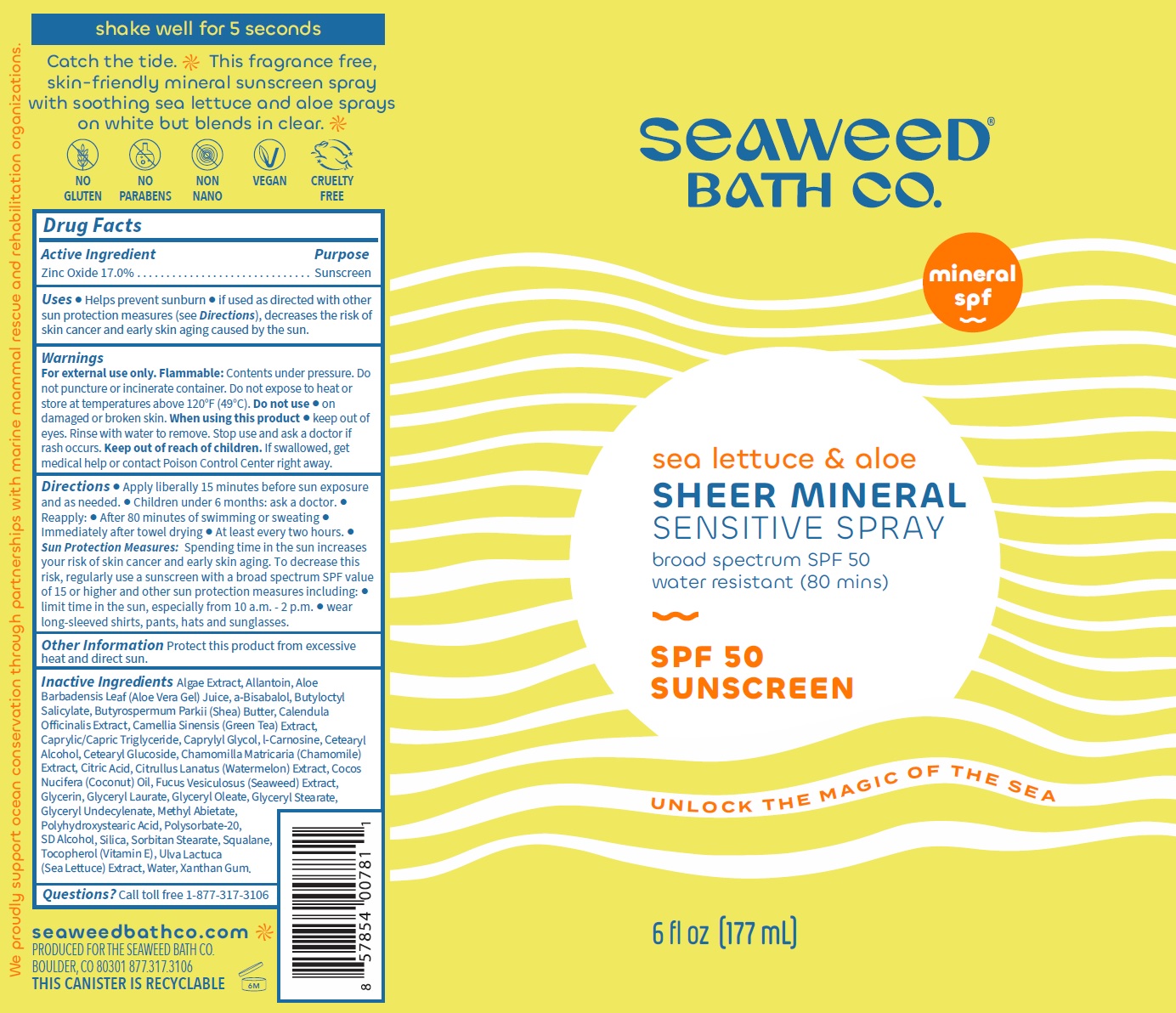 DRUG LABEL: SEAWEED BATH CO. Sheer Mineral Sensitive SPF-50
NDC: 81159-394 | Form: SOLUTION
Manufacturer: The Seaweed Bath Co.
Category: otc | Type: HUMAN OTC DRUG LABEL
Date: 20231106

ACTIVE INGREDIENTS: ZINC OXIDE 170 mg/1 mL
INACTIVE INGREDIENTS: ALLANTOIN; ALOE VERA LEAF; BUTYLOCTYL SALICYLATE; SHEA BUTTER; CALENDULA OFFICINALIS FLOWER; GREEN TEA LEAF; MEDIUM-CHAIN TRIGLYCERIDES; CAPRYLYL GLYCOL; CARNOSINE; CETOSTEARYL ALCOHOL; CETEARYL GLUCOSIDE; CHAMOMILE; WATERMELON; COCONUT OIL; FUCUS VESICULOSUS; GLYCERIN; GLYCERYL LAURATE; GLYCERYL OLEATE; GLYCERYL MONOSTEARATE; METHYL ABIETATE; POLYSORBATE 20; SILICON DIOXIDE; SORBITAN MONOSTEARATE; SQUALANE; TOCOPHEROL; ULVA LACTUCA; WATER; XANTHAN GUM

SEAWEED BATH CO. Sheer Mineral Sensitive Spray SPF-50

Active Ingredient

Zinc Oxide 17.0%

Purpose

Sunscreen

Uses

• Helps prevent sunburn • If used as directed with other sun protection measures (see), decreases the risk of skin cancer and early skin aging caused by the sun. Directions

Warnings

Contents under pressure. Do not puncture or incinerate container. Do not expose to heat or store at temperatures above 120°F (49°C). For external use only. Flammable:

Do not use

• on damaged or broken skin.

When using this product

• keep out of eyes. Rinse with water to remove. Stop use and ask a doctor if rash occurs.

Keep out of reach of children.

If swallowed, get medical help or contact Poison Control Center right away.

Directions

• Apply liberally 15 minutes before sun exposure and as needed. • Children under 6 months: ask a doctor. • Reapply: • After 80 minutes of swimming or sweating • Immediately after towel drying • At least every two hours.

• Spending time in the sun increases your risk of skin cancer and early skin aging. To decrease this risk, regularly use a sunscreen with a broad spectrum SPF value of 15 or higher and other sun protection measures including: • limit time in the sun, especially from 10 a.m. - 2 p.m. • wear long-sleeved shirts, pants, hats and sunglasses. Sun Protection Measures:

Other Information

Protect this product from excessive heat and direct sun.

Inactive Ingredients

Algae Extract, Allantoin, Aloe Barbadensis Leaf (Aloe Vera Gel) Juice, a-Bisabalol, Butyloctyl Salicylate, Butyrospermum Parkii (Shea) Butter, Calendula Officinalis Extract, Camellia Sinensis (Green Tea) Extract, Caprylic/Capric Triglyceride, Caprylyl Glycol, l-Carnosine, Cetearyl Alcohol, Cetearyl Glucoside, Chamomilla Matricaria (Chamomile) Extract, Citric Acid, Citrullus Lanatus (Watermelon) Extract, Cocos Nucifera (Coconut) Oil, Fucus Vesiculosus (Seaweed) Extract, Glycerin, Glyceryl Laurate, Glyceryl Oleate, Glyceryl Stearate, Glyceryl Undecylenate, Methyl Abietate, Polyhydroxystearic Acid, Polysorbate-20, SD Alcohol, Silica, Sorbitan Stearate, Squalane, Tocopherol (Vitamin E), Ulva Lactuca (Sea Lettuce) Extract, Water, Xanthan Gum.

Questions?

Call toll free 1-877-317-3106